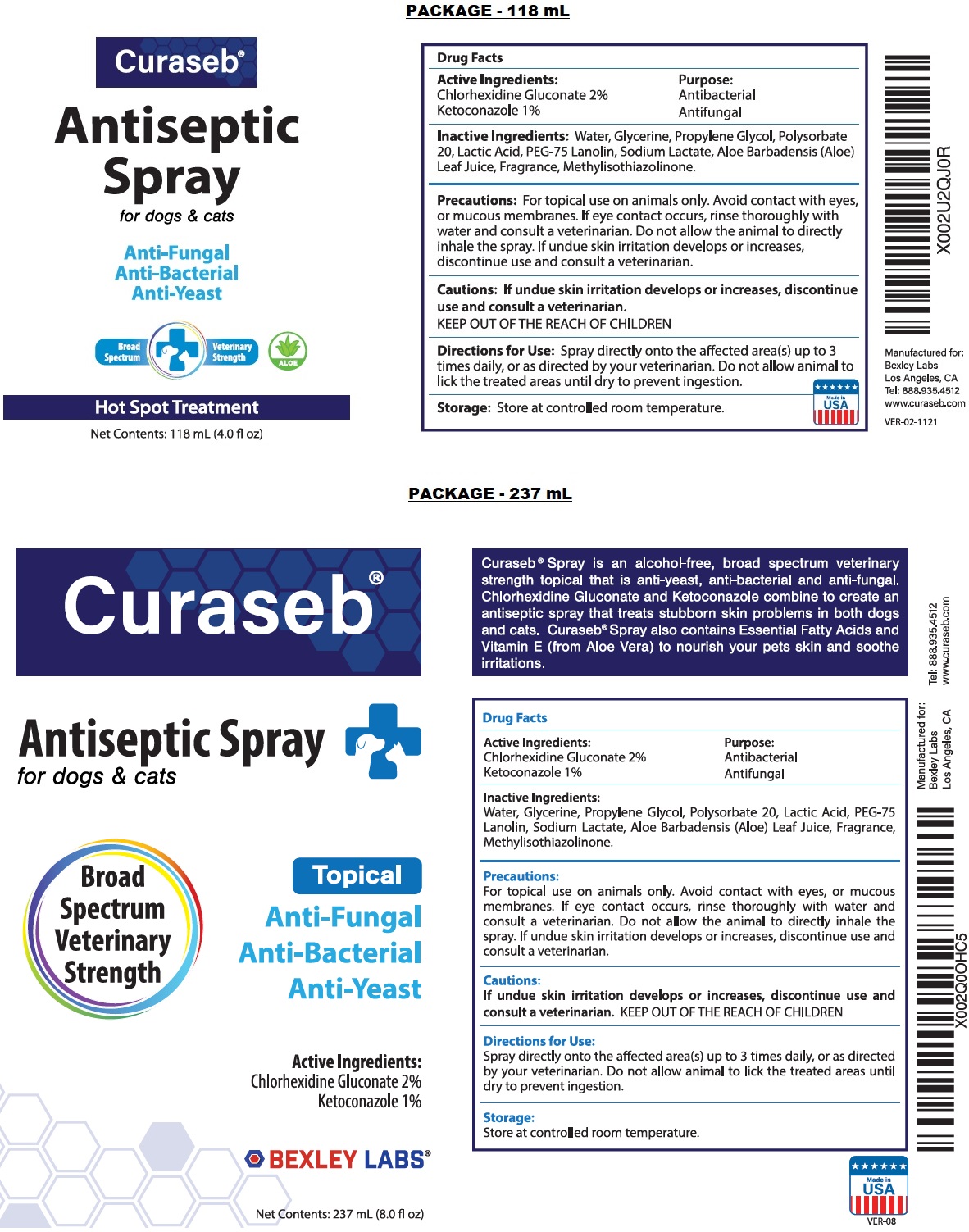 DRUG LABEL: Curaseb Antiseptic
NDC: 86133-101 | Form: SPRAY
Manufacturer: Bexley Labs
Category: animal | Type: OTC ANIMAL DRUG LABEL
Date: 20230222

ACTIVE INGREDIENTS: CHLORHEXIDINE GLUCONATE 2 g/100 mL; KETOCONAZOLE 1 g/100 mL
INACTIVE INGREDIENTS: WATER; GLYCERIN; PROPYLENE GLYCOL; POLYSORBATE 20; LACTIC ACID, UNSPECIFIED FORM; PEG-75 LANOLIN; SODIUM LACTATE; ALOE VERA LEAF; METHYLISOTHIAZOLINONE

Curaseb® Antiseptic Spray

Active Ingredients:

Chlorhexidine Gluconate 2%
Ketoconazole 1%

Purpose:

Antibacterial
Antifungal

INDICATIONS AND USAGE

Curaseb® Spray is an alcohol-free, broad spectrum veterinary strength topical that is anti-yeast, anti-bacterial and anti-fungal. Chlorhexidine Gluconate and Ketoconazole combine to create an antiseptic spray that treats stubborn skin problems in both dogs and cats. Curaseb® Spray also contains Essential Fatty Acids and Vitamin E (from Aloe Vera) to nourish your pets skin and soothe irritations.

Inactive Ingredients:

Water, Glycerin, Propylene Glycol, Polysorbate 20, Lactic Acid, PEG-75 Lanolin, Sodium Lactate, Aloe Barbadensis (Aloe) Leaf Juice, Fragrance, Methylisothiazolinone.

Precautions:

For topical use on animals only. Avoid contact with eyes, or mucous membranes. If eye contact occurs, rinse thoroughly with water and consult a veterinarian. Do not allow the animal to directly inhale the spray.

Cautions:

If undue skin irritation develops or increases, discontinue use and consult a veterinarian.

KEEP OUT OF THE REACH OF CHILDREN

Directions for Use:

Spray directly onto the affected area(s) up to 3 times daily, or as directed by your veterinarian. Do not allow animal to lick the treated areas until dry to prevent ingestion.

Storage:

Store at controlled room temperature.

for dogs & cats

Hot Spot Treatment

Manufactured for:
Bexley Labs
Los Angeles, CA

Tel: 888.935.4512
www.curaseb.com

Made in USA